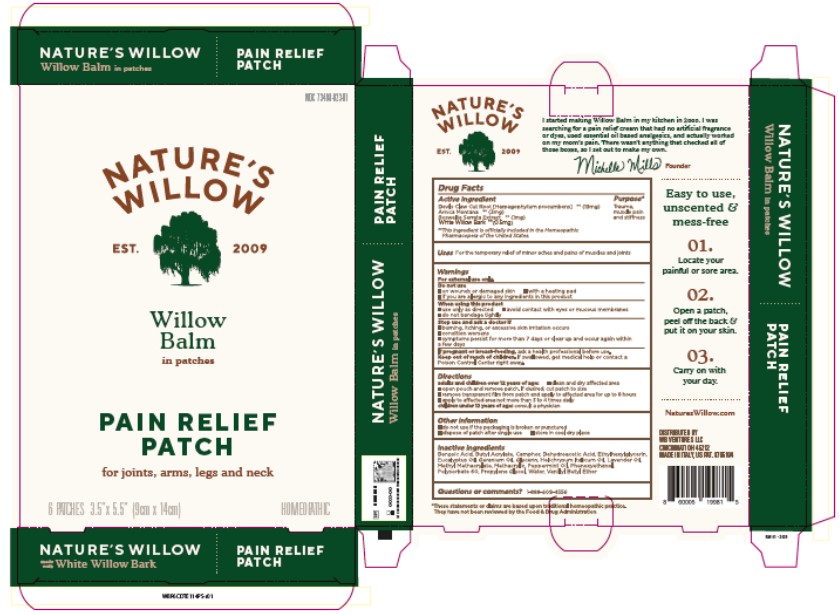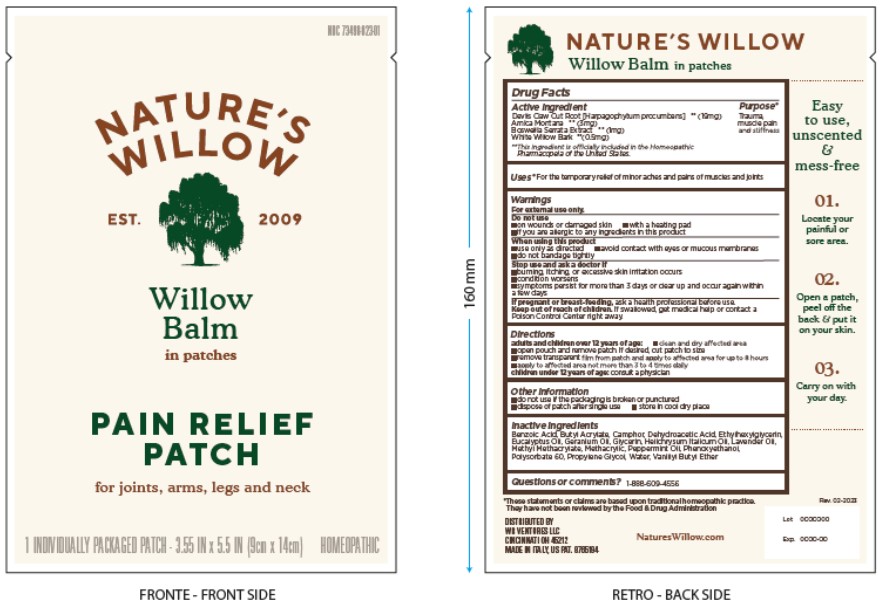 DRUG LABEL: Natures Willow Balm Pain Relieving Patch
NDC: 73498-023 | Form: PATCH
Manufacturer: WB Ventures LLC
Category: homeopathic | Type: HUMAN OTC DRUG LABEL
Date: 20231219

ACTIVE INGREDIENTS: ARNICA MONTANA FLOWER 3 mg/1 1; SALIX ALBA BARK 0.5 mg/1 1; HARPAGOPHYTUM PROCUMBENS ROOT 19 mg/1 1; INDIAN FRANKINCENSE 1 mg/1 1
INACTIVE INGREDIENTS: VANILLYL BUTYL ETHER; HELICHRYSUM ITALICUM FLOWER OIL; CAMPHOR (NATURAL); PHENOXYETHANOL; WATER; DEHYDROACETIC ACID; ETHYLHEXYLGLYCERIN; BENZOIC ACID; POLYSORBATE 60; BUTYL ACRYLATE/METHYL METHACRYLATE/METHACRYLIC ACID COPOLYMER (18000 MW); LAVENDER OIL; PEPPERMINT OIL; PROPYLENE GLYCOL; GLYCERIN; EUCALYPTUS OIL; GERANIUM OIL, ALGERIAN TYPE

Natures Willow Balm Pain Relieving Patch

Active ingredients

Devils Claw Cut Root [Harpagophytum procumbens] **(19mg)

Arnica Montana **(3mg)

Boswellia Serrata Extract **(1mg)

Salix Alba **(0.5mg)

**This ingredient is officially included in the Homeopathic Pharmacopoeia of the United States.

Purpose

Trauma, muscle pain and stiffness

Uses

For the temporary relief of minor aches and pains of muscles and joints

Warnings

For external use only.

Do not use

- on wounds or damaged skin
- with a heating pad
- if you are allergic to any ingredients in this product

When using this product

- use only as directed
- avoid contact with eyes or mucous membranes
- do not bandage tightly

Stop use and ask a doctor if

- burning, itching or excessive skin irritation occurs
- condition worsens
- symptoms persist for more than 3 days or clear up and occur again within a few days

If pregnant or breast-feeding, ask a health professional before use.

Keep out of reach of children. If swallowed, get medical help or contact a Poison Control Center right away.

Directions

adults and children over 12 years of age:

- clean and dry affected area
- open pouch and remove patch. If desired, cut patch to size
- remove transparent film from patch and apply to affected area for up to 8 hours
- apply to affected area not more than 3 to 4 times daily

children under 12 years of age: consult a physician

Other information

- do not use if the packaging is broken or punctured
- dispose of patch after single use
- store in cool dry place

Inactive ingredients

Benzoic Acid, Butyl Acrylate, Camphor, Dehydroacetic Acid, Ethylhexylglycerin, Eucalyptus Oil, Geranium Oil, Glycerin, Helichrysum Italicum Oil, Lavender Oil, Methyl Methacrylate, Methacrylic, Peppermint Oil, Phenoxyethanol, Polysorbate 60, Propylene Glycol, Water, Vanillyl Butyl Ether

Questions or comments?

1-888-609-4556

SPL Unclassified Section

*These statements or claims are based on traditional homeopathic practice. They have not been reviewed by the Food and Drug Administration.